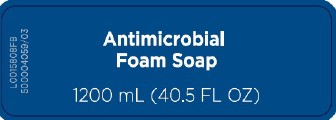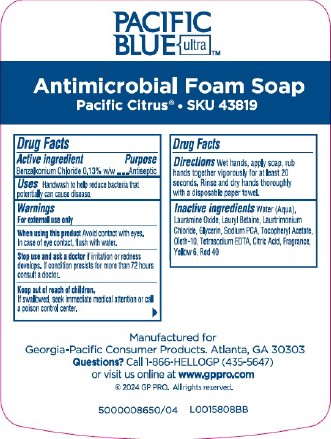 DRUG LABEL: Pacific Blue Ultra Antimicrobial

NDC: 54622-712 | Form: SOAP
Manufacturer: Georgia-Pacific Consumer Products LP
Category: otc | Type: HUMAN OTC DRUG LABEL
Date: 20260204

ACTIVE INGREDIENTS: BENZALKONIUM CHLORIDE 1.3 mg/1 mL
INACTIVE INGREDIENTS: SODIUM PYRROLIDONE CARBOXYLATE; .ALPHA.-TOCOPHEROL ACETATE; OLETH-10; EDETATE SODIUM; CITRIC ACID MONOHYDRATE; FD&C YELLOW NO. 6; FD&C RED NO. 40; LAURAMINE OXIDE; LAURYL BETAINE; LAURTRIMONIUM CHLORIDE; GLYCERIN; WATER

Pacific Blue Ultra 712.001/712AC
Antimicrobial Foam Soap-Pacific Citrus

Active ingredient

Benzalkonium chloride 0.13% w/w

Purpose

Antiseptic

Uses

Handwash to help reduce bacteria that potentially can cause disease.

Warnings

For external use only

When using this product

Avoid contact with eyes. In case of eye contact, flush with water.

Stop use and ask a doctor

if irritation or redness develops. If condition persists for more than 72 hours consult a doctor.

Keep out of reach of children.

If swallowed, seek immediate medical attention or call a poison control center.

Directions

Wet hands, apply soap, rub hand together vigorously for at least 20 seconds. Rinse and dry hand thoroughly with a disposable paper towel.

Inactive ingredients

Water (Aqua), Lauramine Oxide, Lauryl Betaine, Lautrimonium Chloride, Glycerin, Sodium PCA, Tocopheryl Acetate, Oleth-10, Tetrasodium EDTA, Citric Acid, Fragrance, Yellow 6, Red 40

Adverse reaction

Pacific Blue Ultra™

Antimicrobial Foam Soap

Pacific Citrus® - SKU 43819

Manufactured for Georgia-Pacific Consumer Products. Atlanta, GA 30303

Questions? Call 1-866-HELLOGP (435-5647)

or visit us online at www.gppro.com

2024 GP PRO. All rights reserved.

Principal display panel

Antimicrobial Foam Soap

1200 mL (40.5 FL OZ)